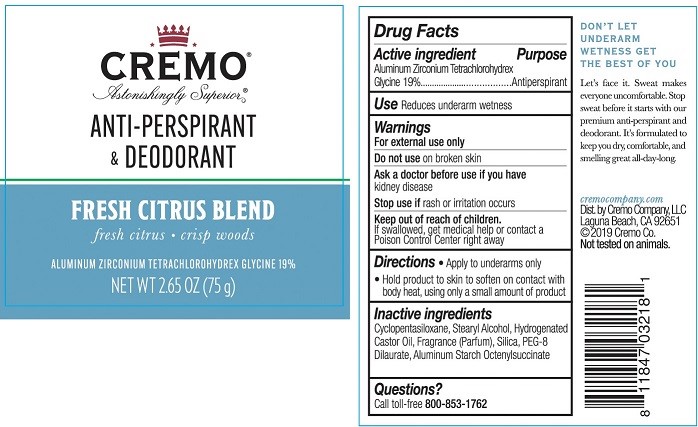 DRUG LABEL: Cremo Anti-Perspirant Deodorant
NDC: 71825-110 | Form: STICK
Manufacturer: Cremo Company
Category: otc | Type: HUMAN OTC DRUG LABEL
Date: 20200103

ACTIVE INGREDIENTS: ALUMINUM ZIRCONIUM TETRACHLOROHYDREX GLY 19 g/100 g
INACTIVE INGREDIENTS: STEARYL ALCOHOL; SILICON DIOXIDE; CYCLOMETHICONE 5; HYDROGENATED CASTOR OIL; PEG-8 DILAURATE; ALUMINUM STARCH OCTENYLSUCCINATE

Cremo Anti-Perspirant - Deodorant Fresh Citrus Blend

Drug Facts

Active ingredient

Aluminum Zirconium Tetrahydrochlorhydrex Glycine 19%

Purpose

Antiperspirant

Use

Reduces underarm wetness

Warnings

For external use only

Do not use on broken skin

Ask a doctor before use if you have kidney disease

Stop use if rash or irritation occurs

Keep out of reach of children. If swallowed, get medical help or contact a Poison Control Center right away

Directions

- Apply to underarms only
- Hold product to skin to soften on contact with body heat, using only a small amount of product

INACTIVE INGREDIENT

Inactive ingredients Cyclopentasiloxane, Stearyl Alcohol, Hydrogenated Castor Oil, Fragrance (Parfum), Silica, PEG-8 Dilaurate, Aluminum Starch Octenylsuccinate

Questions?

Call toll-free 800-853-1762

cremocompany.com

Dist. by Cremo Company, LLC

Laguna Beach, CA 92651

©2019 Cremo Co.

Not tested on animals.

PACKAGE LABEL

CREMO®

Astonishingly Superior®

ANTI-PERSPIRANT & DEODORANT

FRESH CITRUS BLEND

fresh citrus • crisp woods

ALUMINUM ZIRCONIUM TETRACHLOROHYDREX GLYCINE 19%

NET WT 2.65 OZ (75 g)